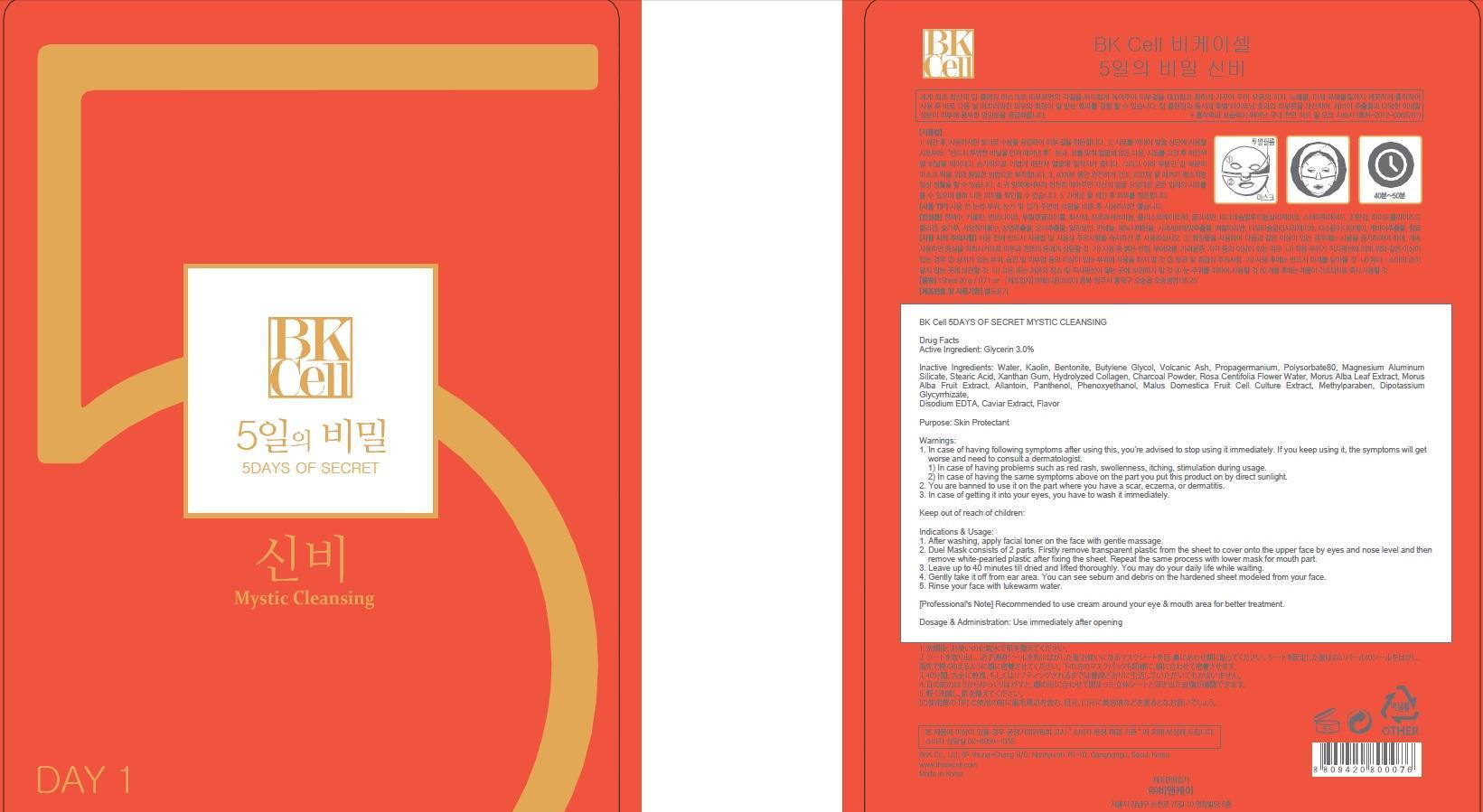 DRUG LABEL: BK Cell 5DAYS OF SECRET MYSTIC CLEANSING
NDC: 69946-010 | Form: PATCH
Manufacturer: BNK CO., LTD.
Category: otc | Type: HUMAN OTC DRUG LABEL
Date: 20150715

ACTIVE INGREDIENTS: Glycerin 0.6 g/20 g
INACTIVE INGREDIENTS: Water; Kaolin

ACTIVE INGREDIENT

Active Ingredient: Glycerin 3.0%

INACTIVE INGREDIENT

Inactive Ingredients: Water, Kaolin, Bentonite, Butylene Glycol, Volcanic Ash, Propagermanium, Polysorbate80, Magnesium Aluminum Silicate, Stearic Acid, Xanthan Gum, Hydrolyzed Collagen, Charcoal Powder, Rosa Centifolia Flower Water, Morus Alba Leaf Extract, Morus Alba Fruit Extract, Allantoin, Panthenol, Phenoxyethanol, Malus Domestica Fruit Cell Culture Extract, Methylparaben, Dipotassium Glycyrrhizate, Disodium EDTA, Caviar Extract, Flavor

PURPOSE

Purpose: Skin Protectant

WARNINGS

Warnings: 1. In case of having following symptoms after using this, you're advised to stop using it immediately. If you keep using it, the symptoms will get worse and need to consult a dermatologist. 1) In case of having problems such as red rash, swollenness, itching, stimulation during usage. 2) In case of having the same symptoms above on the part you put this product on by direct sunlight. 2. You are banned to use it on the part where you have a scar, eczema, or dermatitis. 3. In case of getting it into your eyes, you have to wash it immediately.

KEEP OUT OF REACH OF CHILDREN

Keep out of reach of babies and children

INDICATIONS & USAGE

Indications & Usage: 1. After washing, apply facial toner on the face with gentle massage. 2. Duel Mask consists of 2 parts. Firstly remove transparent plastic from the sheet to cover onto the upper face by eyes and nose level and then remove white-pearled plastic after fixing the sheet. Repeat the same process with lower mask for mouth part. 3. Leave up to 40 minutes till dried and lifted thoroughly. You may do your daily life while waiting. 4. Gently take it off from ear area. You can see sebum and debris on the hardened sheet modeled from your face. 5. Rinse your face with lukewarm water.

[Professional's Note] Recommended to use cream around your eye & mouth area for better treatment.

DOSAGE & ADMINISTRATION

Dosage & Administration: Use immediately after opening